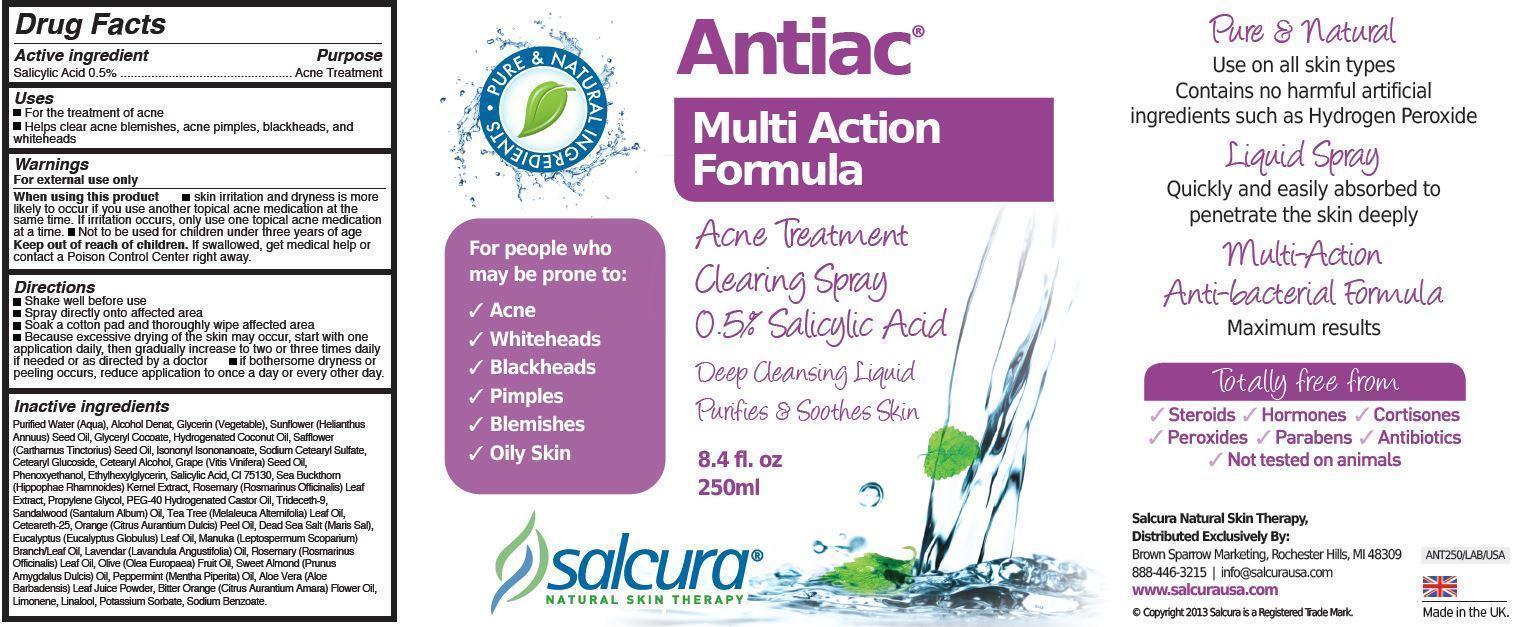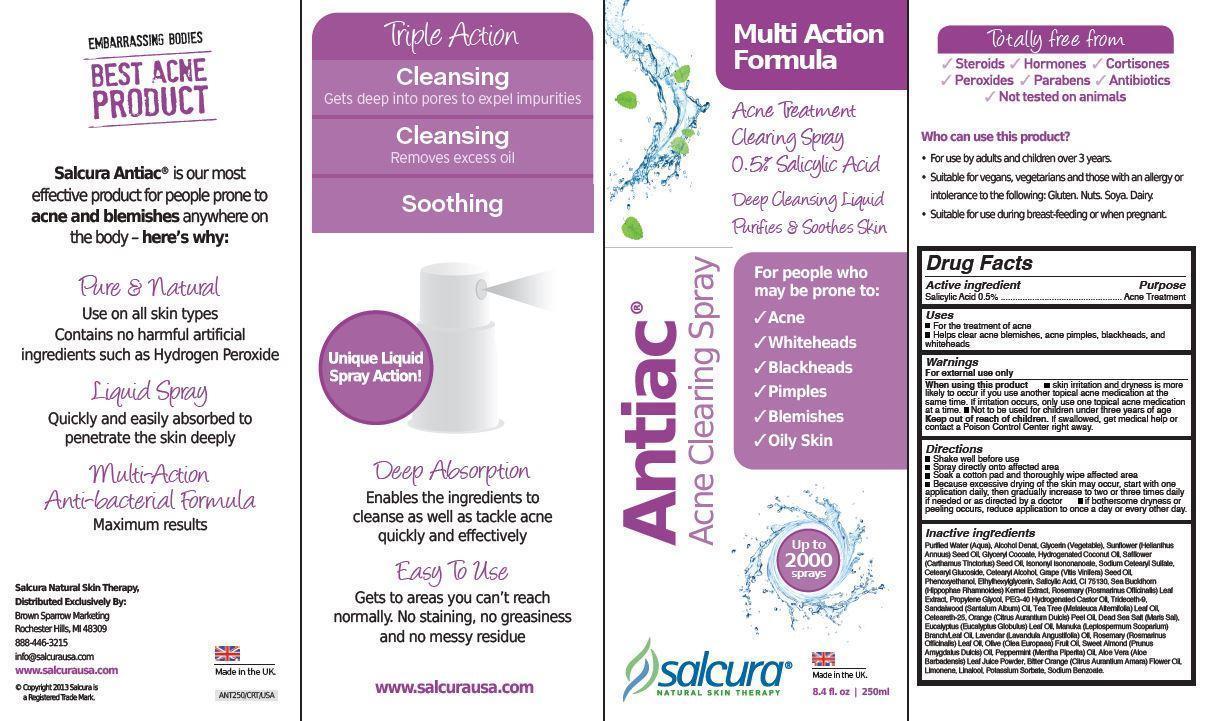 DRUG LABEL: Antiac Acne Clearing
NDC: 58990-000 | Form: SPRAY
Manufacturer: Salcura Ltd
Category: otc | Type: HUMAN OTC DRUG LABEL
Date: 20130724

ACTIVE INGREDIENTS: Salicylic Acid 5 mg/1 mL
INACTIVE INGREDIENTS: WATER; GLYCERIN; SUNFLOWER SEED OIL GLYCERETH-8 ESTERS; GLYCERYL COCOATE; HYDROGENATED COCONUT OIL; ISONONYL ISONONANOATE; SODIUM CETOSTEARYL SULFATE; CETEARYL GLUCOSIDE; GRAPE SEED OIL; PHENOXYETHANOL; ETHYLHEXYLGLYCERIN; Rosemary; Propylene Glycol; POLYOXYL 40 HYDROGENATED CASTOR OIL; TRIDECETH-9; Ceteareth-25; ORANGE OIL; EUCALYPTUS OIL; ROSEMARY OIL; PEPPERMINT OIL; POTASSIUM SORBATE; SODIUM BENZOATE

Antiac Acne Clearing Spray

Active ingredient

Salicylic Acid 0.5%

Purpose

Acne Treatment

Uses

- For the treatment of acne
- Helps clear acne blemishes, acne pimples, blackheads, and
  whiteheads

Warnings

For external use only

When using this product

- skin irritation and dryness is more likely to occur if you use another topical acne medication at thesame time. If irritation occurs, only use one topical acne medication at a time.
- Not to be used for children under three years of age

Keep out of reach of children.

If swallowed, get medical help or contact a Poison Control Center right away.

Directions

- Shake well before use
- Spray directly onto affected area
- Soak a cotton pad and thoroughly wipe affected area
- Because excessive drying of the skin may occur, start with one
  application daily, then gradually increase to two or three times daily
  if needed or as directed by a doctor
- if bothersome dryness or peeling occurs, reduce application to once a day or every other day.

Inactive ingredients

Purified Water (Aqua), Alcohol Denat, Glycerin (Vegetable), Sunflower (Helianthus
Annuus) Seed Oil, Glyceryl Cocoate, Hydrogenated Coconut Oil, Safflower
(Carthamus Tinctorius) Seed Oil, Isononyl Isononanoate, Sodium Cetearyl Sulfate,
Cetearyl Glucoside, Cetearyl Alcohol, Grape (Vitis Vinifera) Seed Oil,
Phenoxyethanol, Ethylhexylglycerin, Salicylic Acid, CI 75130, Sea Buckthorn
(Hippophae Rhamnoides) Kernel Extract, Rosemary (Rosmarinus Officinalis) Leaf
Extract, Propylene Glycol, PEG-40 Hydrogenated Castor Oil, Trideceth-9,
Sandalwood (Santalum Album) Oil, Tea Tree (Melaleuca Alternifolia) Leaf Oil,
Ceteareth-25, Orange (Citrus Aurantium Dulcis) Peel Oil, Dead Sea Salt (Maris Sal),
Eucalyptus (Eucalyptus Globulus) Leaf Oil, Manuka (Leptospermum Scoparium)
Branch/Leaf Oil, Lavendar (Lavandula Angustifolia) Oil, Rosemary (Rosmarinus
Officinalis) Leaf Oil, Olive (Olea Europaea) Fruit Oil, Sweet Almond (Prunus
Amygdalus Dulcis) Oil, Peppermint (Mentha Piperita) Oil, Aloe Vera (Aloe
Barbadensis) Leaf Juice Powder, Bitter Orange (Citrus Aurantium Amara) Flower Oil,
Limonene, Linalool, Potassium Sorbate, Sodium Benzoate.

Inner Label Principal Display

Antiac

Multi Action
Formula

Acne Treatment
Clearing Spray
0. 5% Salicylic Acid
Deep Cleansing Liquid
Purifies & Soothes Skin

8.4 fl. oz
250ml

Pure Natural Ingredients

For people who
may be prone to:
✓ Acne
✓ Whiteheads
✓ Blackheads
✓ Pimples
✓ Blemishes
✓ Oily Skin

salcura
NATRUAL SKIN THERAPY

Pure & Natural
Use on all skin types
Contains no harmful artificial
ingredients such as Hydrogen Peroxide
Liquid Spray
Quickly and easily absorbed to
penetrate the skin deeply
Multi-Action
Anti-bacterial Formula
Maximum results

Totally free from
Steroids Hormones Cortisones
Peroxides Parabens Antibiotics
Not Tested on Animals

Salcura Natural Skin Therapy,
Distributed Exclusively By:
Brown Sparrow Marketing, Rochester Hills, MI 48309
888-446-3215 | info@salcurausa.com
www.salcurausa.com
© Copyright 2013 Salcura is a Registered Trade Mark.

Made in the UK.

Outer Package Principle Display

BEST ACNE PRODUCT

Salcura Antiac® is our most
effective product for people prone to
acne and blemishes anywhere on
the body – here’s why:

Pure & Natural
Use on all skin types
Contains no harmful artificial
ingredients such as Hydrogen Peroxide
Liquid Spray
Quickly and easily absorbed to
penetrate the skin deeply
Multi-Action
Anti-bacterial Formula
Maximum results

Triple Action

Cleansing
Gets deep into pores to expel impurities
Cleansing
Removes excess oil
Soothing

Unique Liquid Spray Action!

Deep Absorption
Enables the ingredients to
cleanse as well as tackle acne
quickly and effectively

Easy To Use
Gets to areas you can’t reach
normally. No staining, no greasiness
and no messy residue

www.salcurausa.com

Up to
2000 sprays

Who can use this product?
• For use by adults and children over 3 years.
• Suitable for vegans, vegetarians and those with an allergy or
intolerance to the following: Gluten. Nuts. Soya. Dairy.
• Suitable for use during breast-feeding or when pregnant.